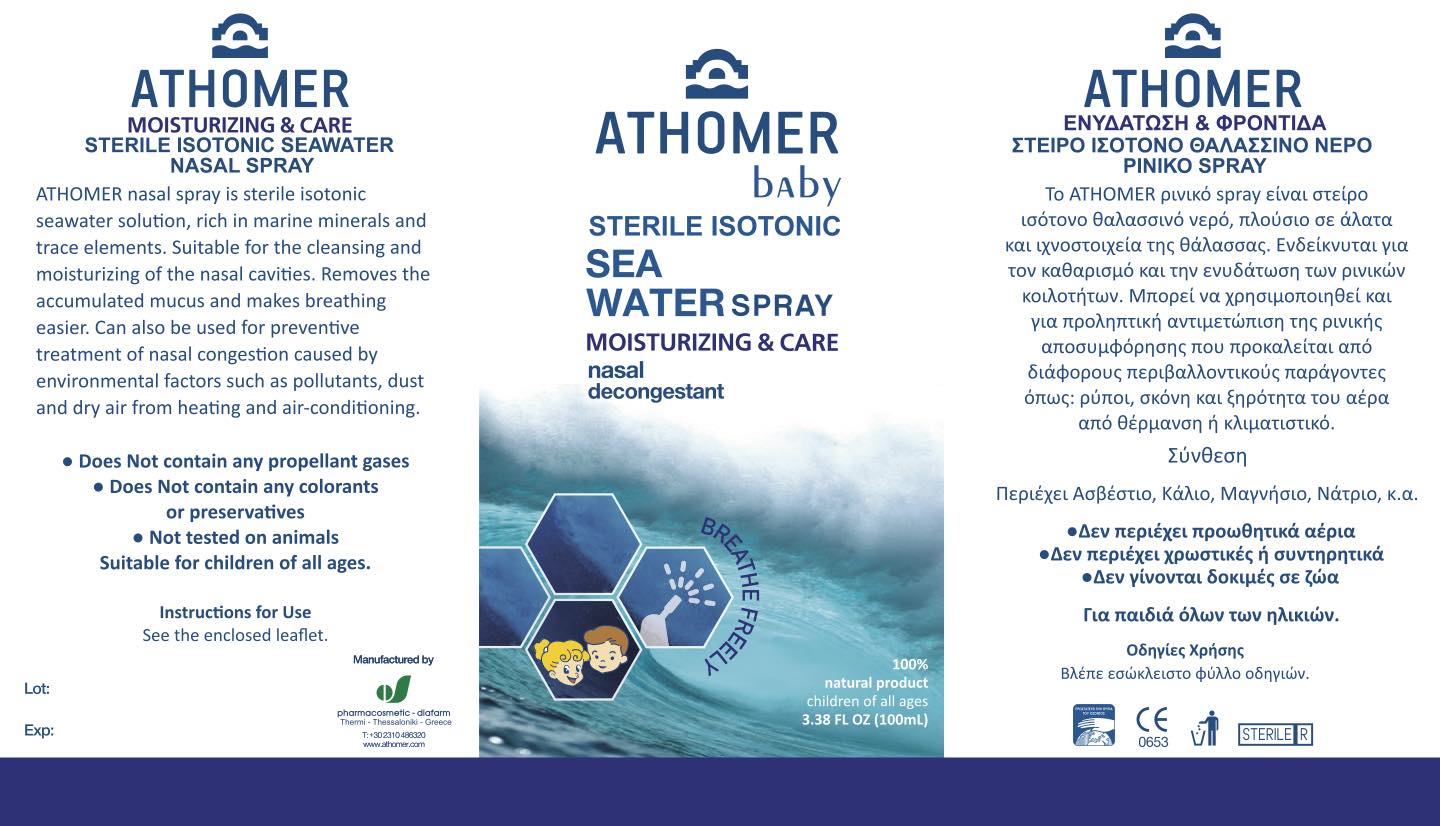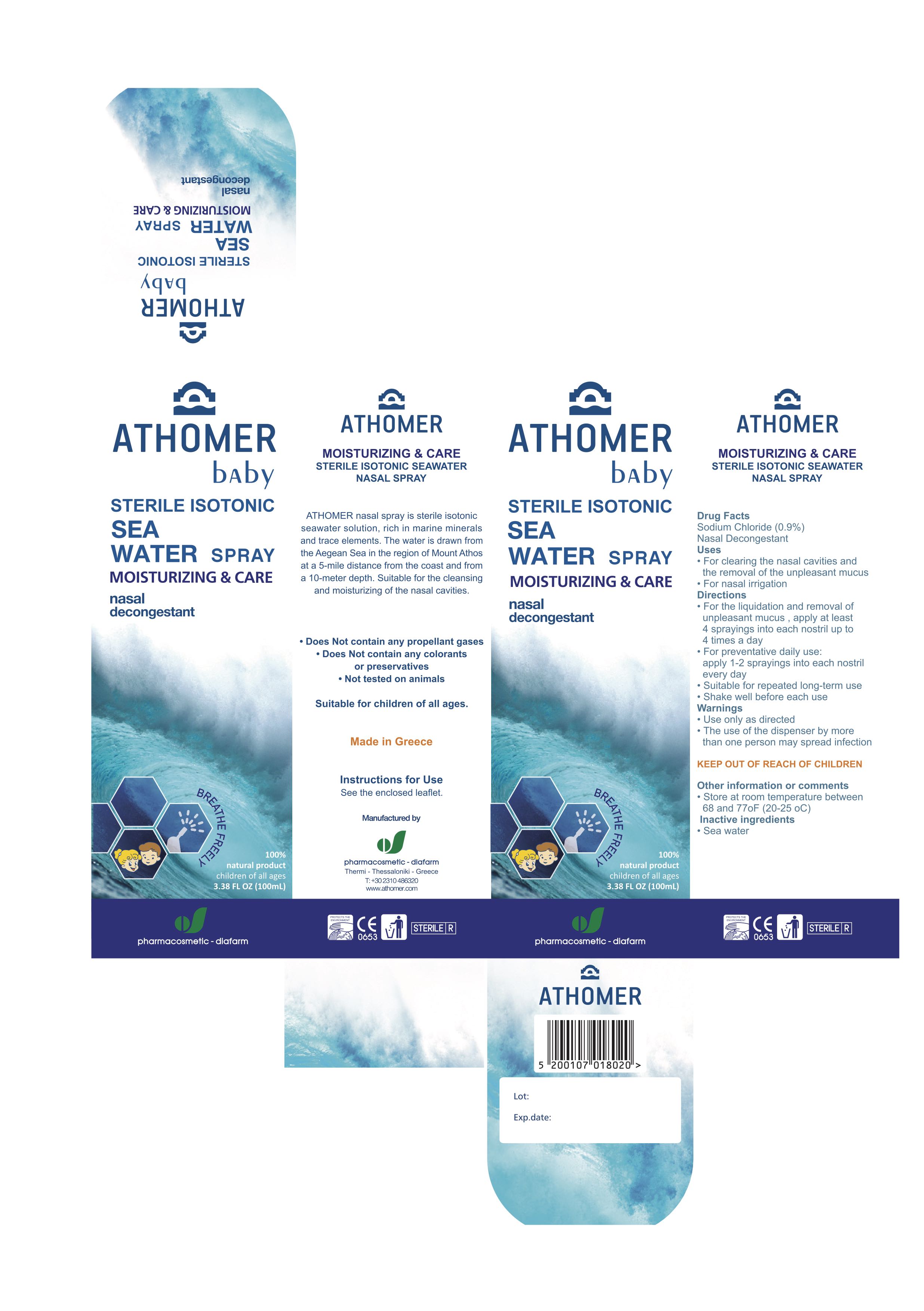 DRUG LABEL: Athomer Baby
NDC: 80897-002 | Form: SPRAY
Manufacturer: Nobu Baby LLC
Category: otc | Type: HUMAN OTC DRUG LABEL
Date: 20230110

ACTIVE INGREDIENTS: SODIUM CHLORIDE 0.9 mg/100 mL
INACTIVE INGREDIENTS: WATER

Athomer Baby Sterile Isotonic Sea Water Spray

Active Ingredient(s)

Sodium Chloride (0.9%)

Purpose

Nasal Decongestant

Use

- For cleaning the nasal cavity and the removal of the unpleasant mucus
- For nasal irrigation

Directions

- For the liquidation and removal of the unpleasant mucus, apply at least 4 sprayings in each nostril up to 4 times per day
- For preventative daily use:

apply 1 to 2 sprayings in each nostril every day

- Suitable for repeated long-term use
- Shake well before each use

Warnings

- Use only as directed
- The use of this dispenser by more than one person may spread infection

Keep out of reach of children

Other information

- Store at room temperature between 68° and 77° F (20° to 25°C)

Inactive ingredients

Sea Water

Package Label - Principal Display Panel

100 ml NDC: 80897-002-10